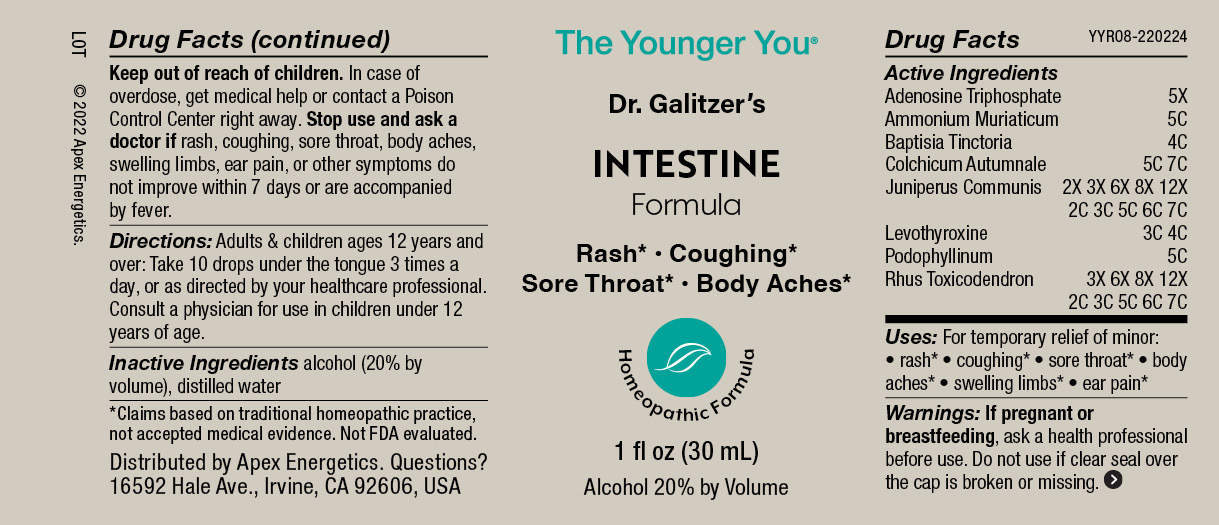 DRUG LABEL: INTESTINE Formula
NDC: 63479-2508 | Form: SOLUTION/ DROPS
Manufacturer: Apex Energetics Inc.
Category: homeopathic | Type: HUMAN OTC DRUG LABEL
Date: 20240108

ACTIVE INGREDIENTS: AMMONIUM CHLORIDE 5 [hp_C]/1 mL; JUNIPER BERRY 7 [hp_C]/1 mL; BAPTISIA TINCTORIA ROOT 4 [hp_C]/1 mL; TOXICODENDRON PUBESCENS LEAF 7 [hp_C]/1 mL; ADENOSINE TRIPHOSPHATE 5 [hp_X]/1 mL; PODOPHYLLUM RESIN 5 [hp_C]/1 mL; COLCHICUM AUTUMNALE BULB 7 [hp_C]/1 mL; LEVOTHYROXINE 4 [hp_C]/1 mL
INACTIVE INGREDIENTS: ALCOHOL; WATER

YYR08

Active Ingredients
Adenosine Triphosphate | 5X
Ammonium Muriaticum | 5C
Baptisia Tinctoria | 4C
Colchicum Autumnale | 5C 7C
Juniperus Communis | 2X 3X 6X 8X 12X 2C 3C 5C 6C 7C
Levothyroxine | 3C 4C
Podophyllinum | 5C
Rhus Toxicodendron | 3X 6X 8X 12X 2C 3C 5C 6C 7C

INDICATIONS AND USAGE

Uses:

For temporary relief of minor:

rash*

coughing*

sore throat*

body aches*

swelling limbs*

ear pain*

*Claims based on traditional homeopathic practice, not accepted medical evidence. Not FDA evaluated.

Warnings:

PREGNANCY OR BREAST FEEDING

If pregnant or breastfeeding, ask a health professional before use.

Do not use if clear seal over the cap is broken or missing.

Keep out of reach of children. In case of overdose, get medical help or contact a Poison Control Center right away.

Stop use and ask a doctor if rash, coughing, sore throat, body aches, swelling limbs, ear pain, or other symptoms do not improve within 7 days or are accompanied by fever.

Directions:

Adults & children ages 12 years and over: Take 10 drops under the tongue 3 times a day, or as directed by your healthcare professional. Consult a physician for use in children under 12 years of age.

Inactive Ingredients

alcohol (20% by volume), distilled water

Distributed by Apex Energetics. Questions?

16592 Hale Ave., Irvine, CA 92606, USA

PACKAGE LABEL

The Younger You®

Dr. Galitzer’s

INTESTINE
Formula

Rash* Coughing*

Sore Throat* Body Aches*

Homeopathic Formula

1 fl oz (30 mL)

Alcohol 20% by Volume